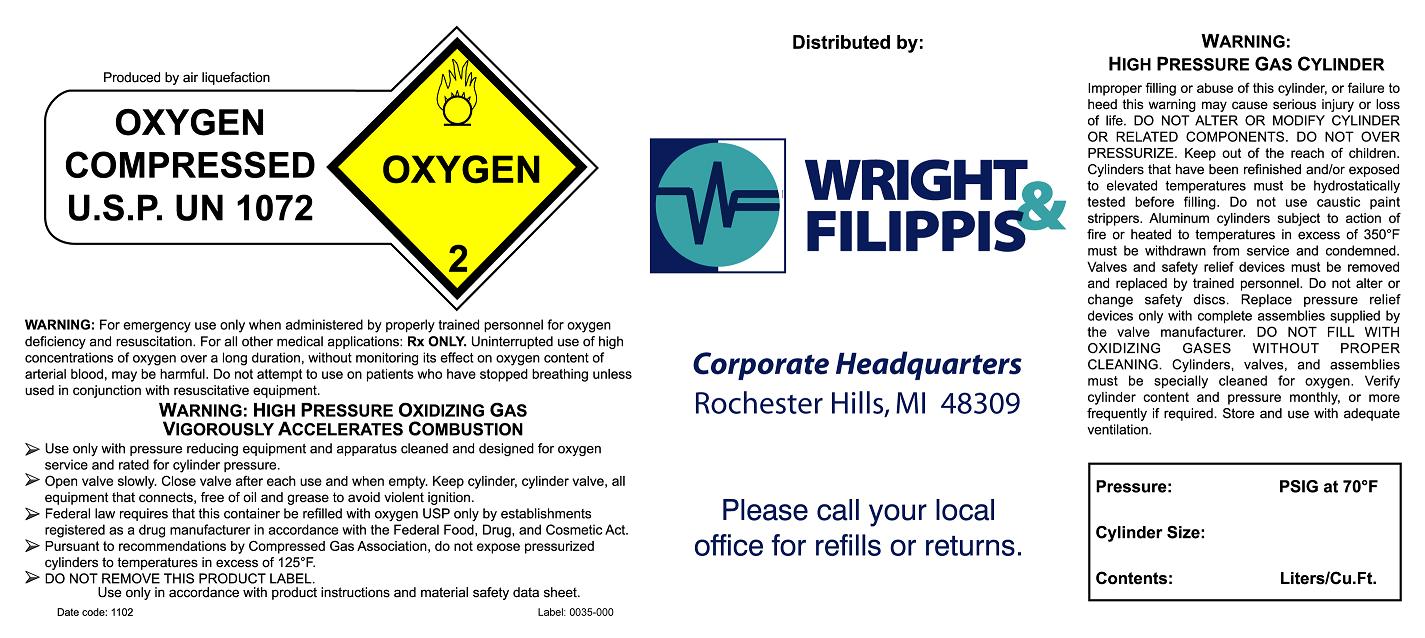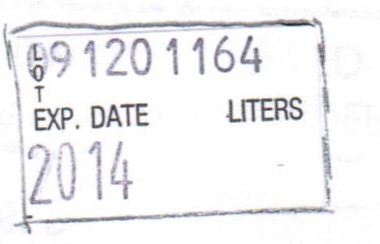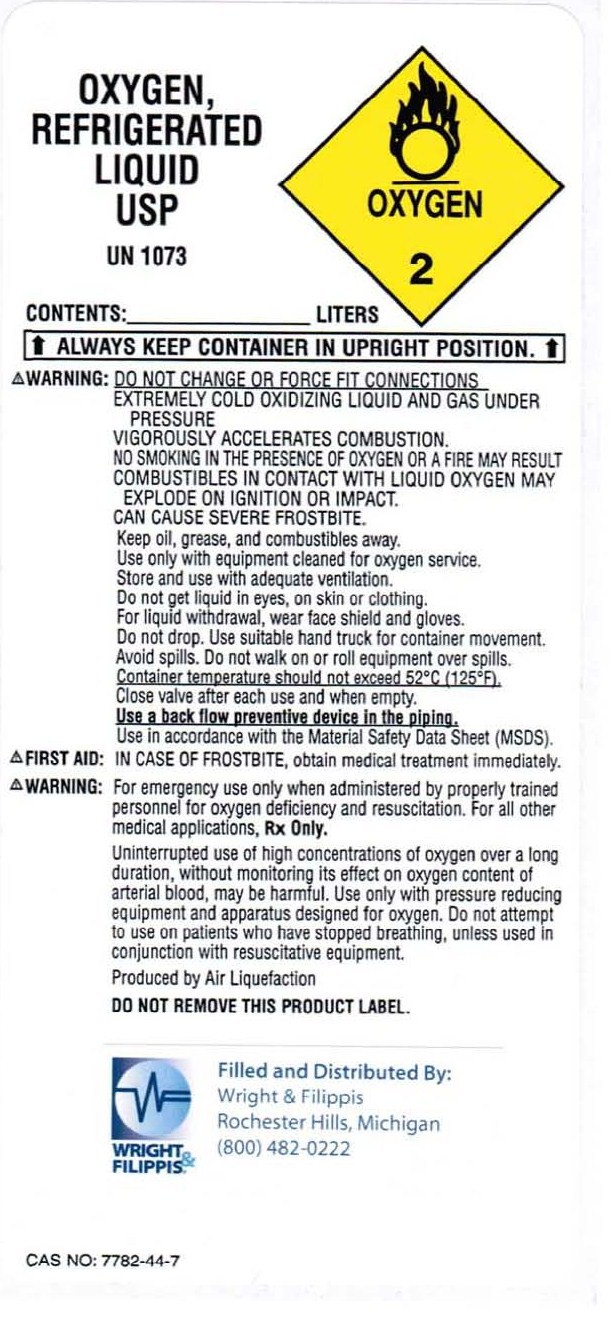 DRUG LABEL: Oxygen
NDC: 62806-0001 | Form: GAS
Manufacturer: Wright & Filippis, Inc.
Category: prescription | Type: HUMAN PRESCRIPTION DRUG LABEL
Date: 20091229

ACTIVE INGREDIENTS: Oxygen 99 L/100 L

Oxygen